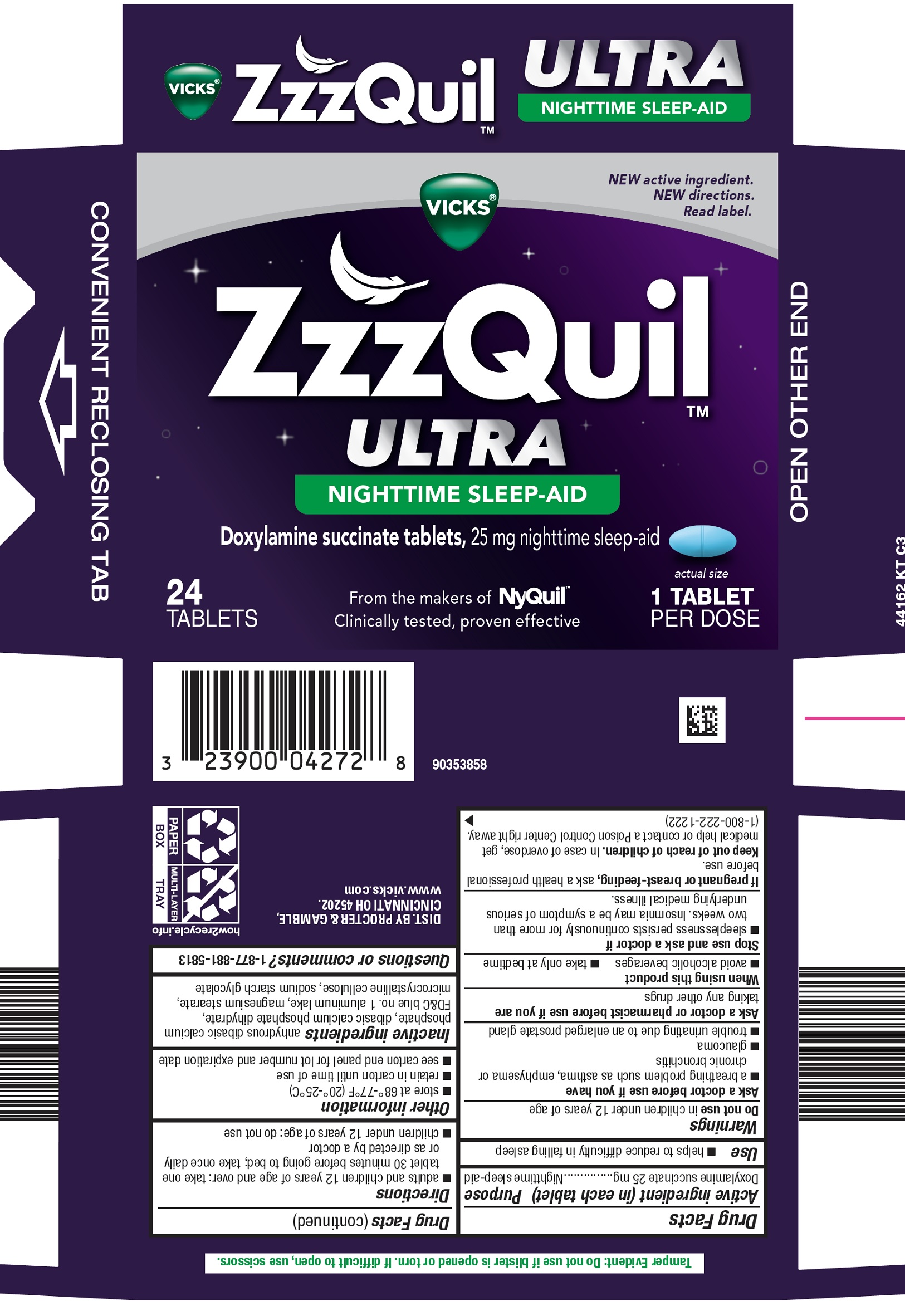 DRUG LABEL: Vicks ZzzQuil
NDC: 69423-902 | Form: TABLET
Manufacturer: The Procter & Gamble Manufacturing Company
Category: otc | Type: HUMAN OTC DRUG LABEL
Date: 20251002

ACTIVE INGREDIENTS: DOXYLAMINE SUCCINATE 25 mg/1 1
INACTIVE INGREDIENTS: CELLULOSE, MICROCRYSTALLINE; SODIUM STARCH GLYCOLATE TYPE A; FD&C BLUE NO. 1 ALUMINUM LAKE; ANHYDROUS DIBASIC CALCIUM PHOSPHATE; DIBASIC CALCIUM PHOSPHATE DIHYDRATE; MAGNESIUM STEARATE

Vicks ZzzQuil Ultra

Drug Facts

Active ingredients (in each tablet)

Doxylamine succinate 25 mg

Purpose

Nighttime sleep-aid

Use

- helps to reduce difficulty in falling asleep

Warnings

Do not use in children under 12 years of age

Ask a doctor before use if you have

- a breathing problem such as asthma, emphysema or chronic bronchitis
- glaucoma
- trouble urinating due to an enlarged prostate gland

Ask a doctor or pharmacist before use if you are taking any other drugs

When using this product

- avoid alcoholic beverages
- take only at bedtime

Stop use and ask a doctor if

- sleeplessness persists continuously for more than two weeks. Insomnia may be a symptom of serious underlying medical illness.

PREGNANCY OR BREAST FEEDING

If pregnant or breast-feeding, ask a health professional before use.

Keep out of reach of children.In case of overdose, get medical help or contact a Poison Control Center right away.

(1-800-222-1222)

Directions

adults & children 12 years of age and over: take one tablet 30 minutes before going to bed; take once daily or as directed by a doctor

children under 12 years of age: do not use

Other information

- store at 68-77° F (20°-25° C)
- retain carton until time of use
- see carton end panel for lot number and expiration date

Inactive ingredients

anhydrous dibasic calcium phosphate, dibasic calcium phosphate dihydrate, FD&C blue no. 1 aluminum lake, magnesium stearate,
microcrystalline cellulose, sodium starch glycolate

Questions?

1-877-881-5813

Tamper Evident:Do not use if blister is opened or torn. If difficult to open, use scissors.

DIST. BY PROCTER & GAMBLE

CINCINNATI OH 45202.

PRINCIPAL DISPLAY PANEL - 24 Tablet Carton

NEW active ingredient.

NEW directions.

Read label.

VICKS ®

ZzzQuil™
ULTRA
NIGHTTIME SLEEP-AID
Doxylamine succinate tablets, 25 mg nighttime sleep-aid

24 TABLETS

From the makers of NyQuil

Clinically tested, proven effective

actual size

1 TABLET

PER DOSE